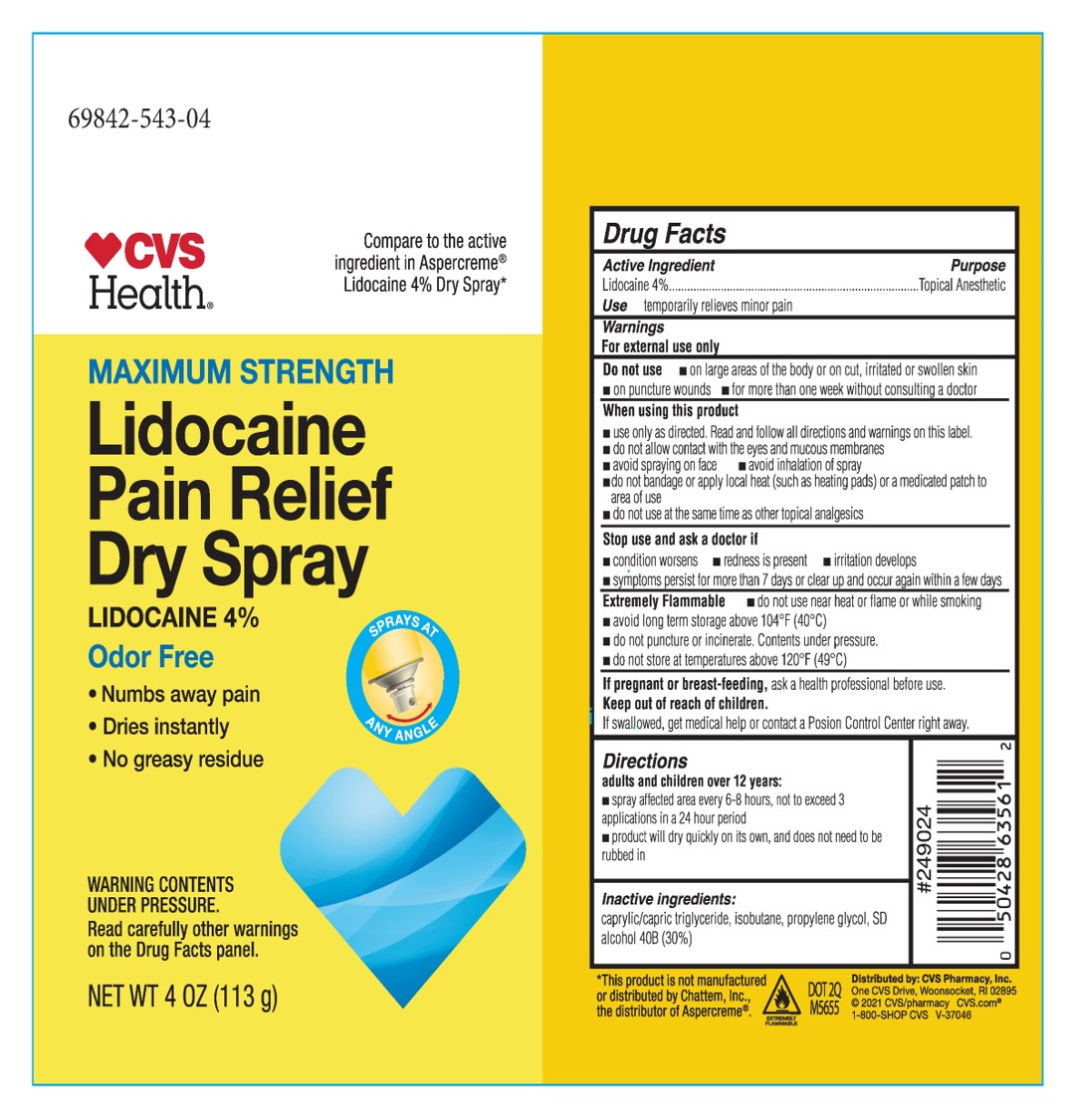 DRUG LABEL: Lidocaine Dry
NDC: 69842-543 | Form: SPRAY
Manufacturer: CVS
Category: otc | Type: HUMAN OTC DRUG LABEL
Date: 20241216

ACTIVE INGREDIENTS: LIDOCAINE 4 g/100 mL
INACTIVE INGREDIENTS: PROPYLENE GLYCOL; MEDIUM-CHAIN TRIGLYCERIDES; ALCOHOL

CVS 4% Lidocaine spray

Active Ingredient

Lidocaine 4%

Use

temporarily relieves minor pain

Warnings

For external use only

Do not use

- On large areas of the body or on cut, irritated or swollen skin.
- On puncture wounds
- for more than one week without consulting a doctor

When using this product

- Use only as directed. Read and follow all directions and warnings on this label
- do not allow contact with the eyes and mucous membranes
- avoid spraying on face
- avoid inhalation of spray
- do not bandage or apply local heatl(such as heating pads) or a medicated patch to area of use
- do not use at the same time as other topical analgesics

Stop use and as a doctor if

- condition worsens
- redness is present
- irritation develops
- symptoms perisist for more than 7 days or clear up and occur again within a few days.

Extremely Flammable

- do not use near heat or flame or while smoking
- avoid long term storage above 104°F (40°C)
- do not puncture or incinerate. Contents under pressure.
- do not store at temperatures above 120°F (49°C)

If pregnant or breast-feeding

ask a health professional before use.

Keep out of reach of children

If swallowed, get medical help or contact a Poison Control Center right away.

Directions

adults and children over 12 years:

- spray affected area every 6 to 8 hours, not to exceed 3 applications in a 24 hour period
- product will dry quickly on its own, and does not need to be rubbed in

children 12 years or younger: ask a doctor

Inactive Ingredients

caprylic/capric triglyceride, isobutane, propylene glycol, alcohol 40B (30%)